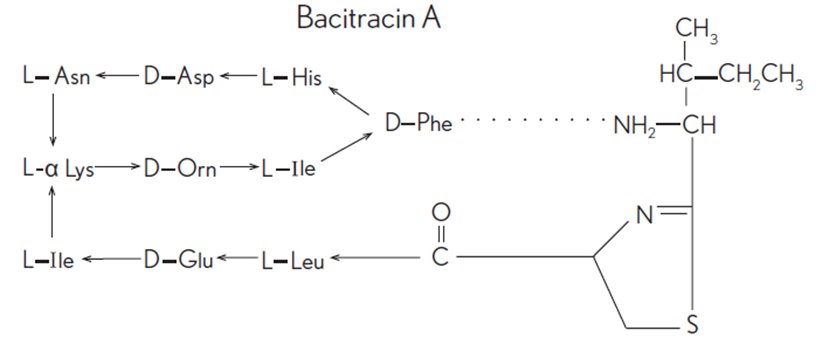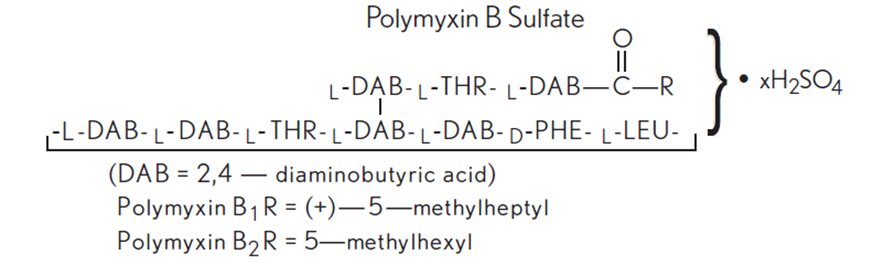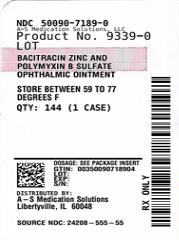 DRUG LABEL: Bacitracin Zinc and Polymyxin B Sulfate
NDC: 50090-7189 | Form: OINTMENT
Manufacturer: A-S Medication Solutions
Category: prescription | Type: HUMAN PRESCRIPTION DRUG LABEL
Date: 20260113

ACTIVE INGREDIENTS: BACITRACIN ZINC 500 [USP'U]/1 g; POLYMYXIN B SULFATE 10000 [USP'U]/1 g
INACTIVE INGREDIENTS: PETROLATUM; PARAFFINUM LIQUIDUM

Bacitracin Zinc and Polymyxin B Sulfate
Ophthalmic Ointment, USP
(Sterile)
Rx only

DESCRIPTION

Bacitracin zinc and polymyxin B sulfate ophthalmic ointment, USP is a sterile antimicrobial ointment formulated for ophthalmic use.

Bacitracin zinc is the zinc salt of bacitracin, a mixture of related cyclic polypeptides (mainly bacitracin A) produced by the growth of an organism of the licheniformis group of Bacillus subtilisvar Tracy. It has a potency of not less than 40 bacitracin units/mg. The structural formula for bacitracin A is:

Polymyxin B sulfate is the sulfate salt of polymyxin B1and B2, which are produced by the growth of Bacillus polymyxa(Prazmowski) Migula (Fam. Bacillaceae). It has a potency of not less than 6,000 polymyxin B units/mg, calculated on an anhydrous basis. The structural formulae are:

Each gram contains: Actives:bacitracin zinc equal to 500 bacitracin units and polymyxin B sulfate equal to 10,000 polymyxin B units; Inactives:mineral oil and white petrolatum.

CLINICAL PHARMACOLOGY

Polymyxin B sulfate attacks gram-negative bacilli, including virtually all strains of Pseudomonas aeruginosaand Haemophilus influenzaespecies.

Bacitracin is active against most gram-positive bacilli and cocci including hemolytic streptococci.

INDICATIONS AND USAGE

For the treatment of superficial ocular infections involving the conjunctiva and/or cornea caused by organisms susceptible to bacitracin zinc and polymyxin B sulfate.

CONTRAINDICATIONS

This product is contraindicated in those individuals who have shown hypersensitivity to any of its components.

WARNINGS

Ophthalmic ointments may retard corneal healing.

PRECAUTIONS

As with other antibiotic preparations, prolonged use may result in overgrowth of nonsusceptible organisms, including fungi. Appropriate measures should be taken if this occurs.

ADVERSE REACTIONS

To report SUSPECTED ADVERSE REACTIONS, contact Bausch & Lomb Incorporated at 1-800-553-5340 or FDA at 1-800-FDA-1088 or www.fda.gov/medwatch.

DOSAGE AND ADMINISTRATION

Apply the ointment every 3 or 4 hours for 7 to 10 days, depending on the severity of the infection.

FOR OPHTHALMIC USE ONLY

HOW SUPPLIED

Product: 50090-7189

NDC: 50090-7189-0 3.5 g in a TUBE / 144 in a CASE